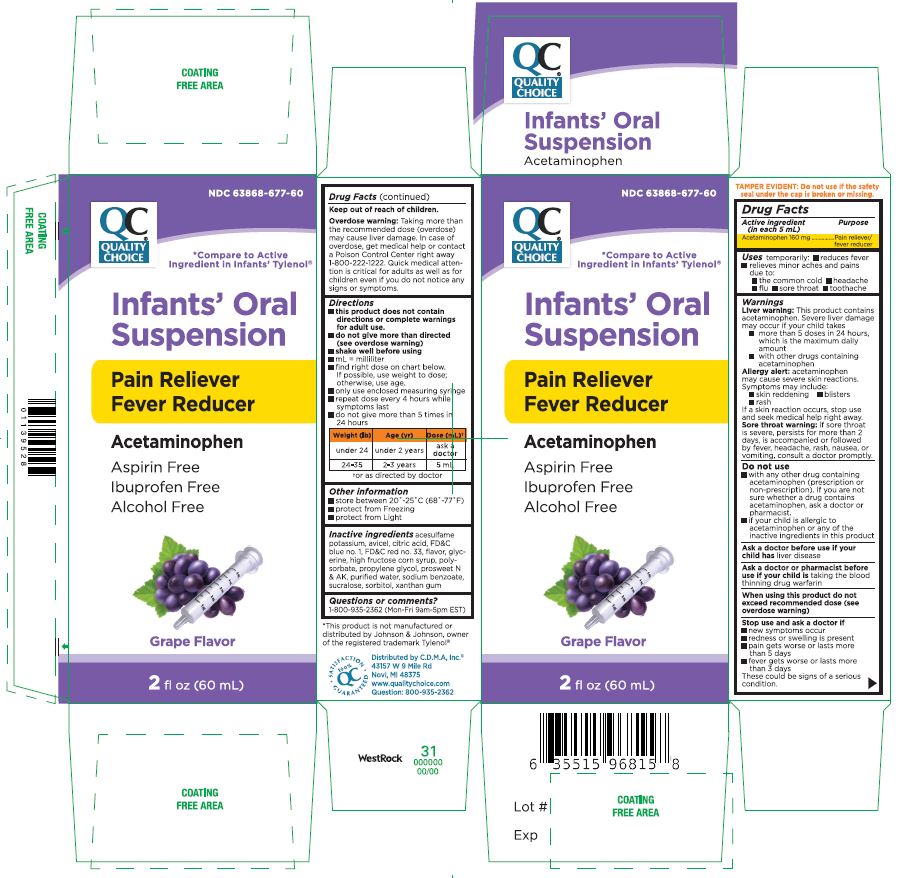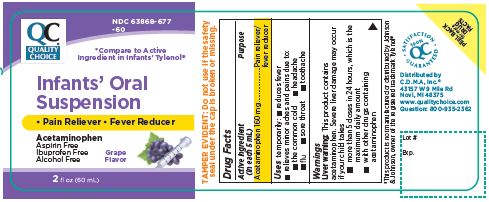 DRUG LABEL: ACETAMINOPHEN
NDC: 63868-677 | Form: SUSPENSION
Manufacturer: CHAIN DRUG MARKETING ASSOCIATION INC
Category: otc | Type: HUMAN OTC DRUG LABEL
Date: 20241226

ACTIVE INGREDIENTS: ACETAMINOPHEN 160 mg/5 mL
INACTIVE INGREDIENTS: ACESULFAME POTASSIUM; MICROCRYSTALLINE CELLULOSE; CITRIC ACID MONOHYDRATE; FD&C BLUE NO. 1; GLYCERIN; HIGH FRUCTOSE CORN SYRUP; POLYSORBATE 20; PROPYLENE GLYCOL; WATER; SODIUM BENZOATE; SUCRALOSE; SORBITOL; XANTHAN GUM

Infants' Oral Suspension
Pain Reliever
Fever Reducer
Acetaminophen
Grape Flavor

Active Ingredient Purpose (in each 5 mL)

Acetaminophen 160 mg ............... Pain reliever/fever reducer

PURPOSE

- Pain reliever
- fever reducer

Uses temporarily:

- reduces fever
- relieves minor aches and pains

due to:

- the common cold
- headache
- flu
- sore throat
- toothache

Warnings

Liver warning: This product contains acetaminophen. Severe liver damage may occur if your child takes

- more than 5 doses in 24 hours, which is the maximum daily amount
- with other drugs containing acetaminophen

Allergy alert: acetaminophen may cause severe skin reactions. Symptoms may include:

- skin reddening
- blisters
- rash

If a skin reaction occurs, stop use and seek medical help right away.

Sore throat warning: if sore throat is severe, persists for more than 2 days, is accompanied or followed by fever, headache, rash, nausea, or
vomiting, consult a doctor promptly.

When using this product do not exceed recommended dose (see overdose warning)

Do not use

- with any other drug containing acetaminophen (prescription or non-prescription). If you are not sure whether a drug contains acetaminophen, ask a doctor or pharmacist.
- if your child is allergic to acetaminophen or any of the inactive ingredients in this product

Ask a doctor before use if your child has liver disease

Ask a doctor or pharmacist before use if your child is taking the blood thinning drug warfarin

Stop use and ask a doctor if

- new symptoms occur
- redness or swelling is present
- pain gets worse or lasts more than 5 days
- fever gets worse or lasts more than 3 days

These could be signs of a serious condition.

Keep out of reach of children.

OVERDOSAGE

Overdose warning: Taking more than the recommended dose (overdose) may cause liver damage. In case of overdose, get medical help or contact a Poison Control Center right away 1-800-222-1222. Quick medical attention is critical for adults as well as for children even if you do not notice any signs or symptoms.

Directions

- this product does not contain directions or complete warnings for adult use.
- do not give more than directed (see overdose warning)
- shake well before using
- ml= milliliter
- find right dose on chart below.

If possible, use weight to dose; otherwise, use age.

- only use enclosed measuring syringe
- repeat dose every 4 hours while symptoms last
- do not give more than 5 times in 24 hours
  Weight (Ib) | Age (yr) | Dose (mL) [or as directed by doctor]
  Under 24 | Under 2 years | Ask a doctor
  24-35 | 2-3 years | 5 mL

Other information

- store between 20° -25°c (68°-77 °F)
- protect from freezing
- protect from light

Questions or comments?
1-800-935-2362 (Mon-Fri 9am-5pm EST)

Inactive ingredients

acesulfame potassium, avicel, citric acid, FD&C blue no. 1, FD&C red no. 33, flavor, glycerine, high fructose corn syrup, polysorbate, propylene glycol, prosweet N & AK, purified water, sodium benzoate, sucralose, sorbitol, xanthan gum

"This product is not manufactured or distributed by Johnson & Johnson, owner of the registered trademark Tylenol®

Distributed by C.D.M.A. lnc.
43157 W 9 Mile Rd
Novi, MI 48375
www.qualitychoice.com
Question: 800-935-2362